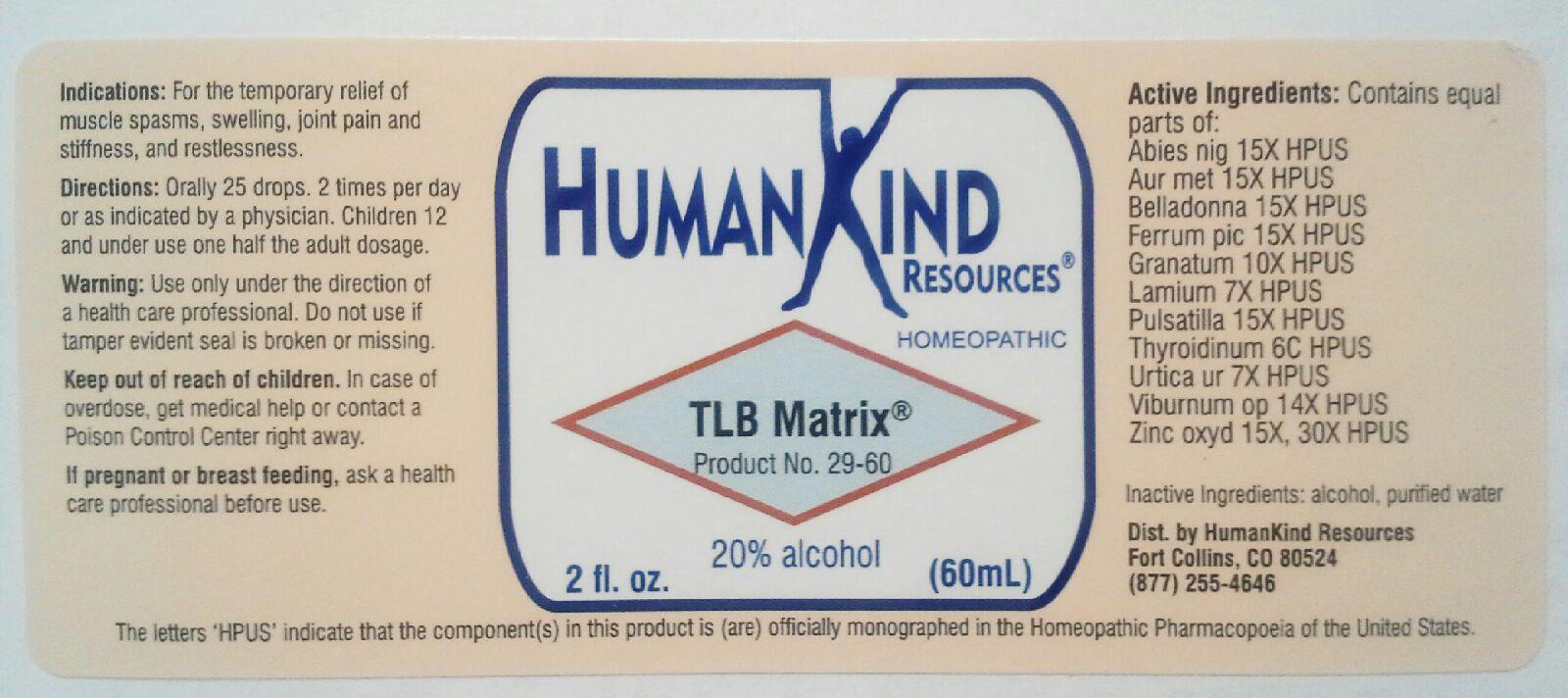 DRUG LABEL: TLB-Matrix
NDC: 64616-107 | Form: LIQUID
Manufacturer: Vitality Works, Inc.
Category: homeopathic | Type: HUMAN OTC DRUG LABEL
Date: 20251217

ACTIVE INGREDIENTS: PICEA MARIANA RESIN 15 [hp_X]/1 mL; GOLD 15 [hp_X]/1 mL; ATROPA BELLADONNA 15 [hp_X]/1 mL; FERRIC PICRATE 15 [hp_X]/1 mL; PUNICA GRANATUM ROOT BARK 10 [hp_X]/1 mL; LAMIUM ALBUM 7 [hp_X]/1 mL; PULSATILLA VULGARIS 15 [hp_X]/1 mL; THYROID, UNSPECIFIED 6 [hp_C]/1 mL; URTICA URENS 7 [hp_X]/1 mL; VIBURNUM OPULUS BARK 14 [hp_X]/1 mL; ZINC OXIDE 30 [hp_X]/1 mL
INACTIVE INGREDIENTS: ALCOHOL; WATER

TLB-Matrix

TLB-Matrix

Abies Nigra 15X Pulsatilla 15X

Arum Metallicum 15X Thyroidinum 6C

Belladonna 15X Urtica Urens 7X

Ferrum Picricum 15X Viburnum Opulus 14X

Granatum 10X Zinc Oxydatum 15X, 30X

Lamium Album 7X

TLB-Matrix

Alcohol, Purified Water

TLB-Matrix

Use only under the direction of a health care professional. Do not use if tamper evident seal is broken or missing.

TLB-Matrix

Keep out of reach of children. In case of overdose, get medical help or contact a Poison Control Center right away.

TLB-Matrix

For the temporary relief of muscle spasms, swelling, joint pain and stiffness, and restlessness.

TLB-Matrix

Orally 25 drops, 2 times per day or as indicated by a physician. Children 12 and under use one half the adult dosage.

TLB-Matrix

Eases joint instability or dysfunction.